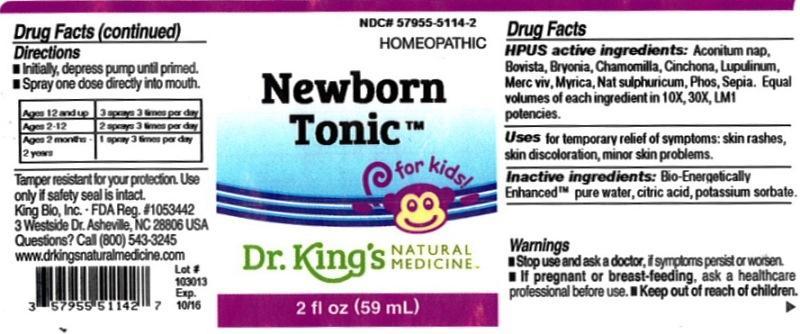 DRUG LABEL: Newborn Tonic
NDC: 57955-5114 | Form: LIQUID
Manufacturer: King Bio Inc.
Category: homeopathic | Type: HUMAN OTC DRUG LABEL
Date: 20140321

ACTIVE INGREDIENTS: ACONITUM NAPELLUS 10 [hp_X]/59 mL; LYCOPERDON UTRIFORME FRUITING BODY 10 [hp_X]/59 mL; BRYONIA ALBA ROOT 10 [hp_X]/59 mL; MATRICARIA RECUTITA 10 [hp_X]/59 mL; CINCHONA OFFICINALIS BARK 10 [hp_X]/59 mL; HOPS 10 [hp_X]/59 mL; MERCURY 10 [hp_X]/59 mL; MORELLA CERIFERA ROOT BARK 10 [hp_X]/59 mL; SODIUM SULFATE 10 [hp_X]/59 mL; PHOSPHORUS 10 [hp_X]/59 mL; SEPIA OFFICINALIS JUICE 10 [hp_X]/59 mL
INACTIVE INGREDIENTS: WATER; CITRIC ACID MONOHYDRATE; POTASSIUM SORBATE

Newborn Tonic™

ACTIVE INGREDIENT

Drug Facts__________________________________________________________________________________________________________

HPUS active ingredients: Aconitum napellus, Bovista, Bryonia, Chamomilla, Cinchona officinalis, Lupulinum, Mercurius vivus, Myrica cerifera, Natrum sulphuricum, Phosphorus, Sepia. Equal volumes of each ingredient in 10X, 30X, LM1 potencies.

INDICATIONS AND USAGE

Uses for temporary relief of symptoms: skin rashes, skin discoloration, minor skin problems.

Inactive Ingredients:

Bio-Energetically Enhanced™ pure water, citric acid and potassium sorbate.

Warnings

- Stop use and ask a doctor, if symptoms persist or worsen.

- If pregnant or breast-feeding, ask a healthcare professional before use.

- Keep out of reach of children

DOSAGE AND ADMINISTRATION

- Initially, depress pump until primed.
- Spray one dose directly into mouth.
- Ages 12 and up - 3 sprays 3 times per day.
- Ages 2-12 - 2 sprays 3 times per day.
- Ages 2 months-2 years - 1 spray 3 times per day.

OTHER SAFETY INFORMATION

Tamper resistant for your protection. Use only if safety seal is intact.

PURPOSE

Uses for temporary relief of symptoms:

- skin rashes
- skin discoloration
- minor skin problems